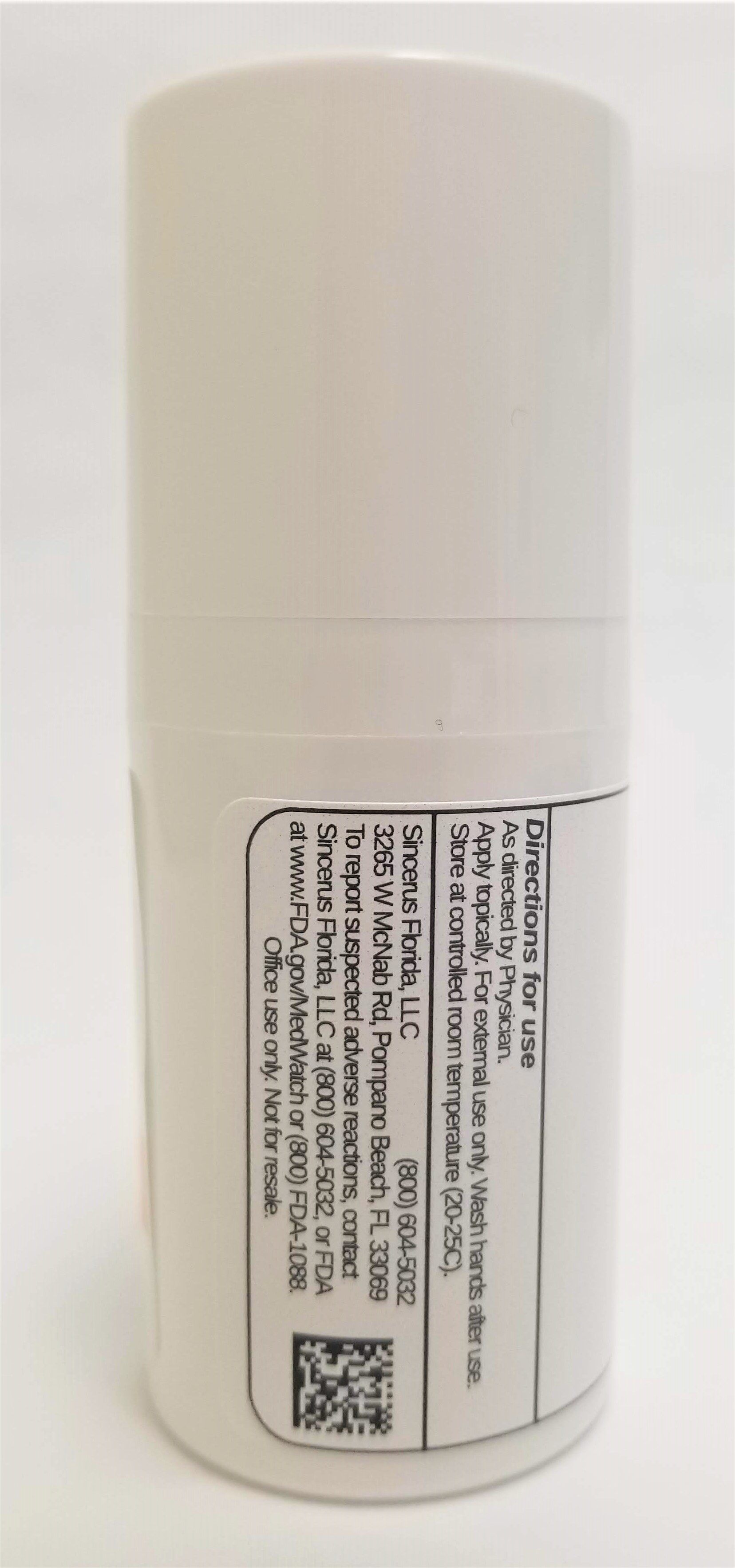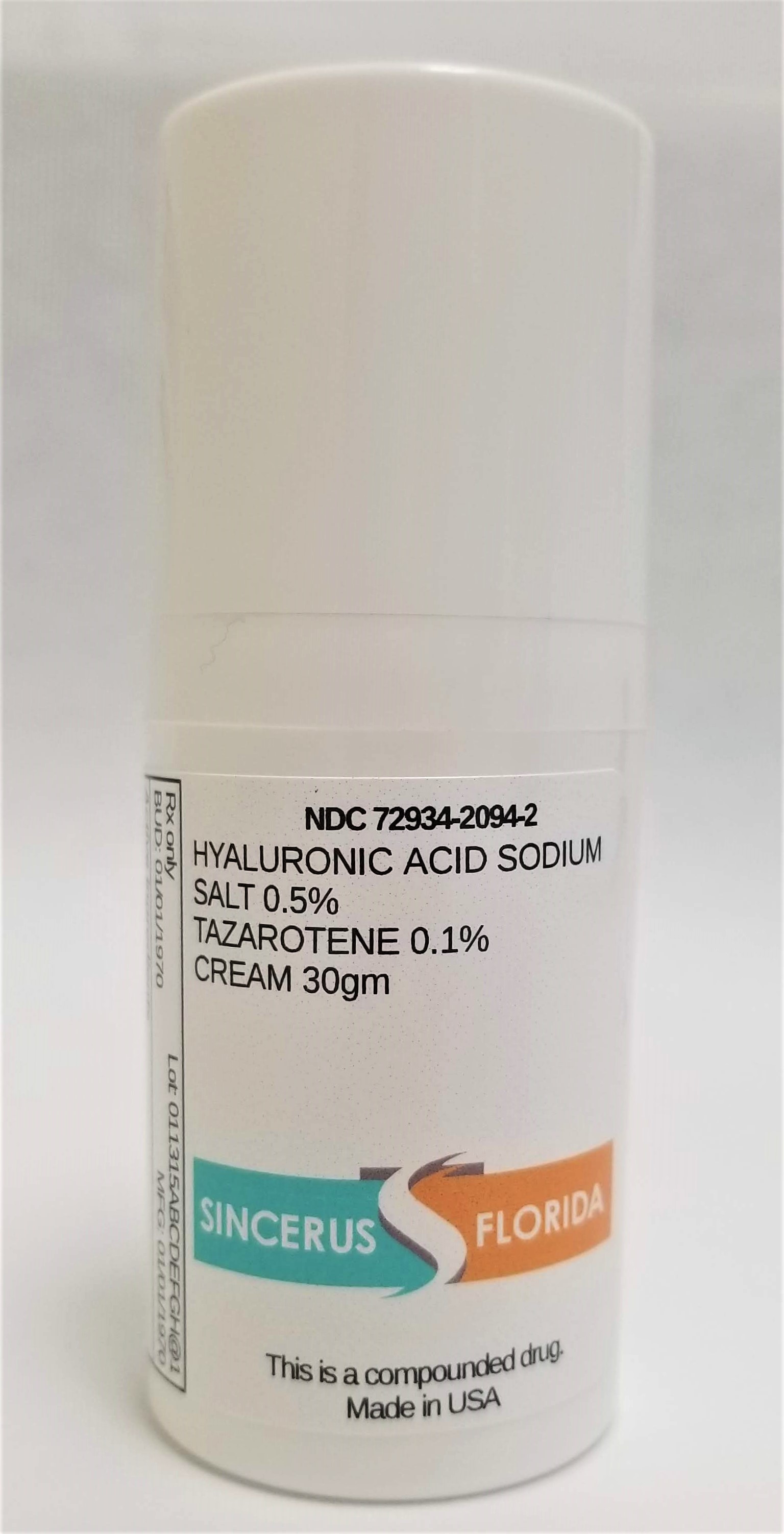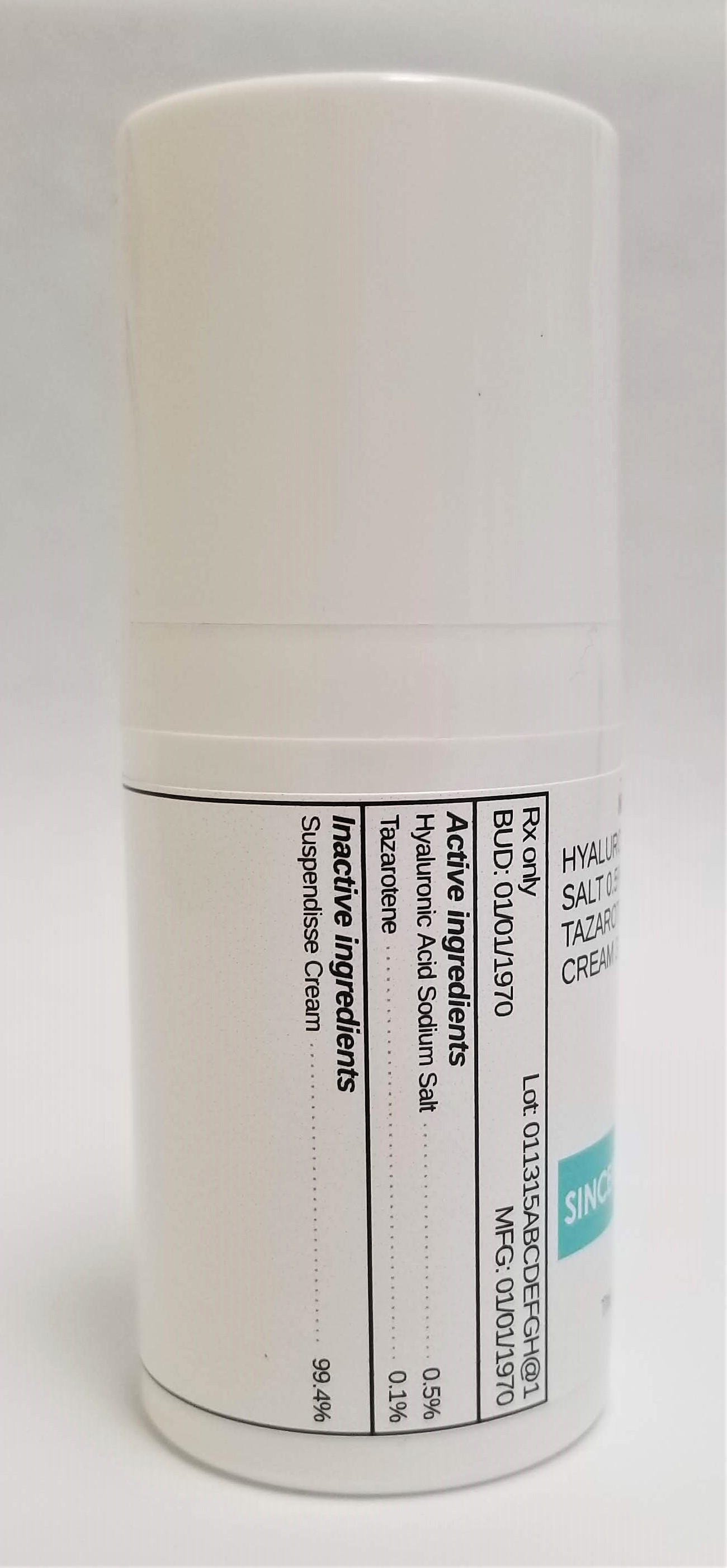 DRUG LABEL: HYALURONIC ACID SODIUM SALT 0.5% / TAZAROTENE 0.1%
NDC: 72934-2094 | Form: CREAM
Manufacturer: Sincerus Florida, LLC
Category: prescription | Type: HUMAN PRESCRIPTION DRUG LABEL
Date: 20190506

ACTIVE INGREDIENTS: HYALURONATE SODIUM 0.5 g/100 g; TAZAROTENE 0.1 g/100 g

HYALURONIC ACID SODIUM SALT 0.5% / TAZAROTENE 0.1%